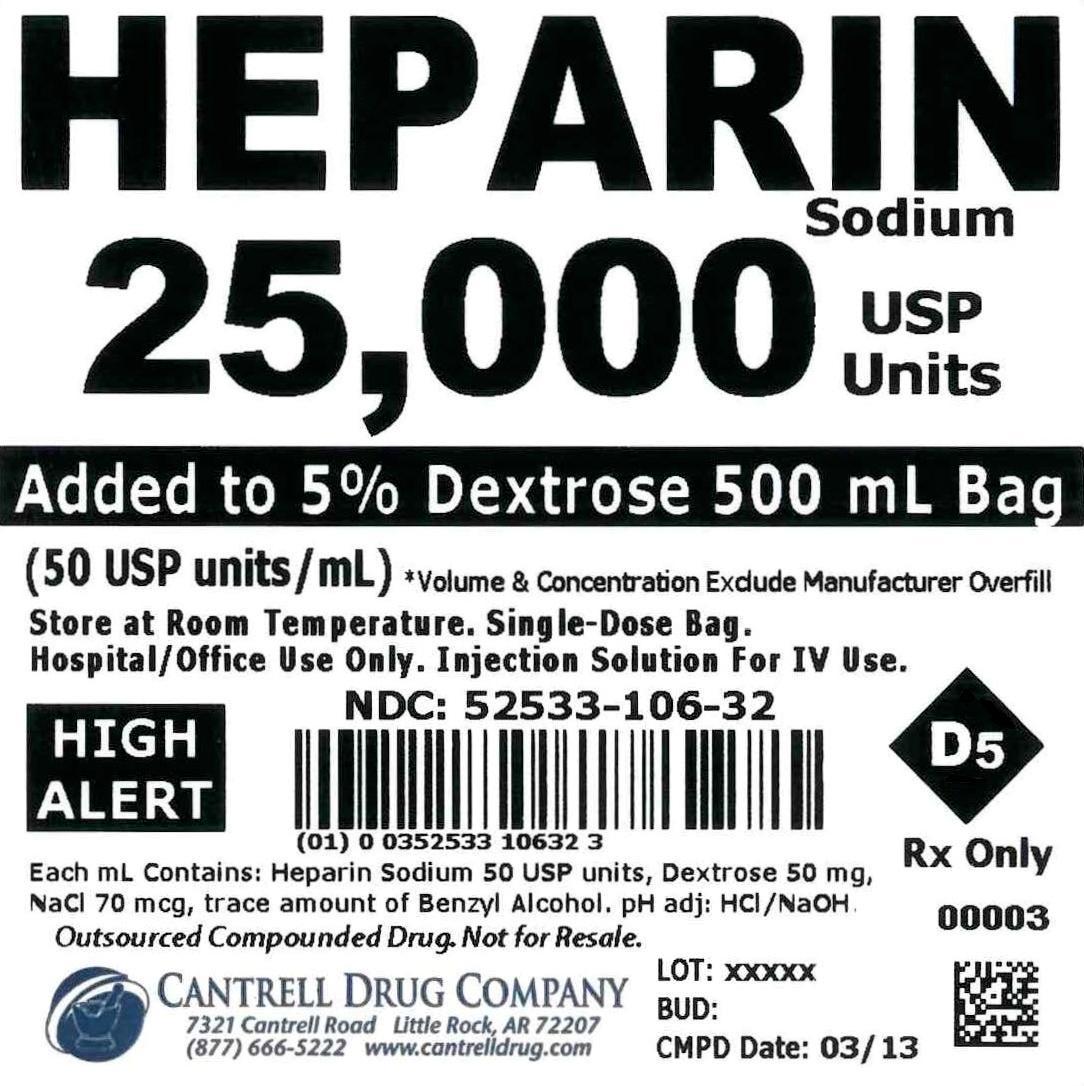 DRUG LABEL: Heparin Sodium
NDC: 52533-106 | Form: INJECTION, SOLUTION
Manufacturer: Cantrell Drug Company
Category: prescription | Type: HUMAN PRESCRIPTION DRUG LABEL
Date: 20141224

ACTIVE INGREDIENTS: Heparin Sodium 50 [USP'U]/1 mL
INACTIVE INGREDIENTS: DEXTROSE 50 mg/1 mL; BENZYL ALCOHOL 0.0001 mL/1 mL; Water

Heparin Sodium 25,000 USP Units Added to 5% Dextrose 500 mL Bag